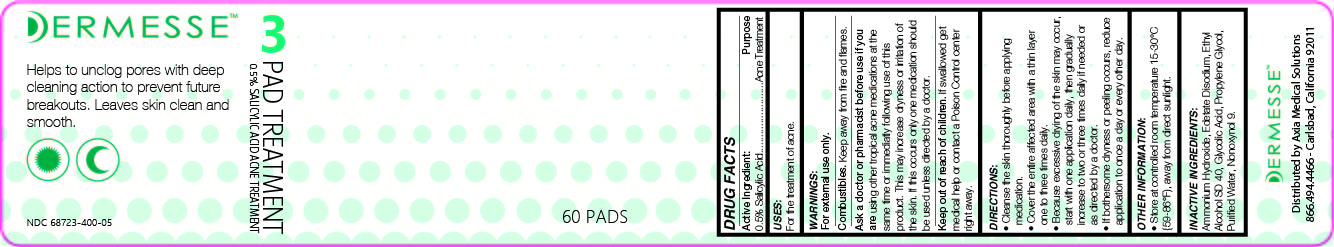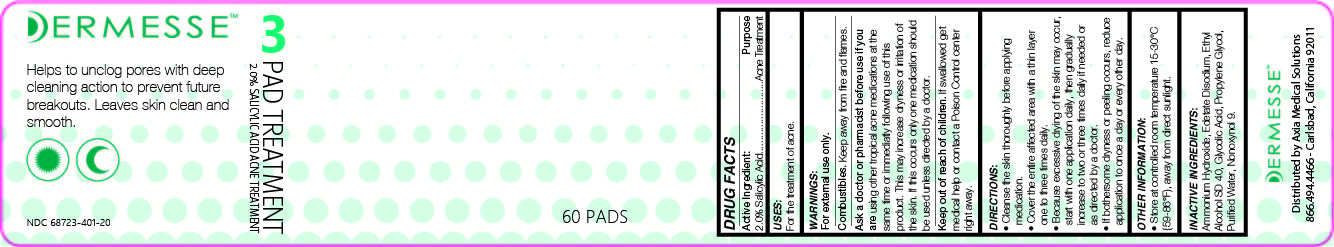 DRUG LABEL: Dermesse Pad Treatment 0.5
NDC: 68723-400 | Form: LOTION
Manufacturer: Axia Medical Solutions, LLC
Category: otc | Type: HUMAN OTC DRUG LABEL
Date: 20220111

ACTIVE INGREDIENTS: SALICYLIC ACID 0.5 g/1 1
INACTIVE INGREDIENTS: EDETATE DISODIUM; GLYCOLIC ACID; PROPYLENE GLYCOL; NONOXYNOL-9; WATER; AMMONIA; ALCOHOL

Dermesse Pad Treatment

Active Ingredients

0.5% Salicylic Acid

2% Salicylic Acid

Purpose

Acne Treatment

Uses:

For the treatment of acne

Warninigs:

For external use only

Combustibles. Keep away from fire or flames.

Ask a doctor or pharmacist before use if you are:

using other topical acne medications at the same time or immediately following use of this product. This may increase dryness or irritation of the skin. If this occurs only one medication should be used unless directed by a doctor.

Keep out of reach of children

If swallowed get medical help or contact a Poison Control center right away.

DIRECTIONS:

- Cleanse the skin thoroughly before applying medication
- Cover the entire affected area with a thin layer one to three times daily.
- Because excessive drying of the skin may occur, start with one application daily, then gradually increase to two or three times daily if needed or directed by a doctor.
- If bothersome dryness or peeling occurs, reduce application to once a day or every other day.

OTHER INFORMATION:

Store at controlled room temperature 15-30^0C (59-86^0F), away from diret sunlight.

INACTIVE INGREDIENTS:

Ammonium Hydroxide, Edetate Disodium, Ethyl Alcohol SD40, Glycolic Acid, Propylene Glycol, Purified Water, Nonoxynol 9.

PACKAGE LABEL

Dermesse Pad Treatment 0.5

Dermesse Pad Treatment 2.0